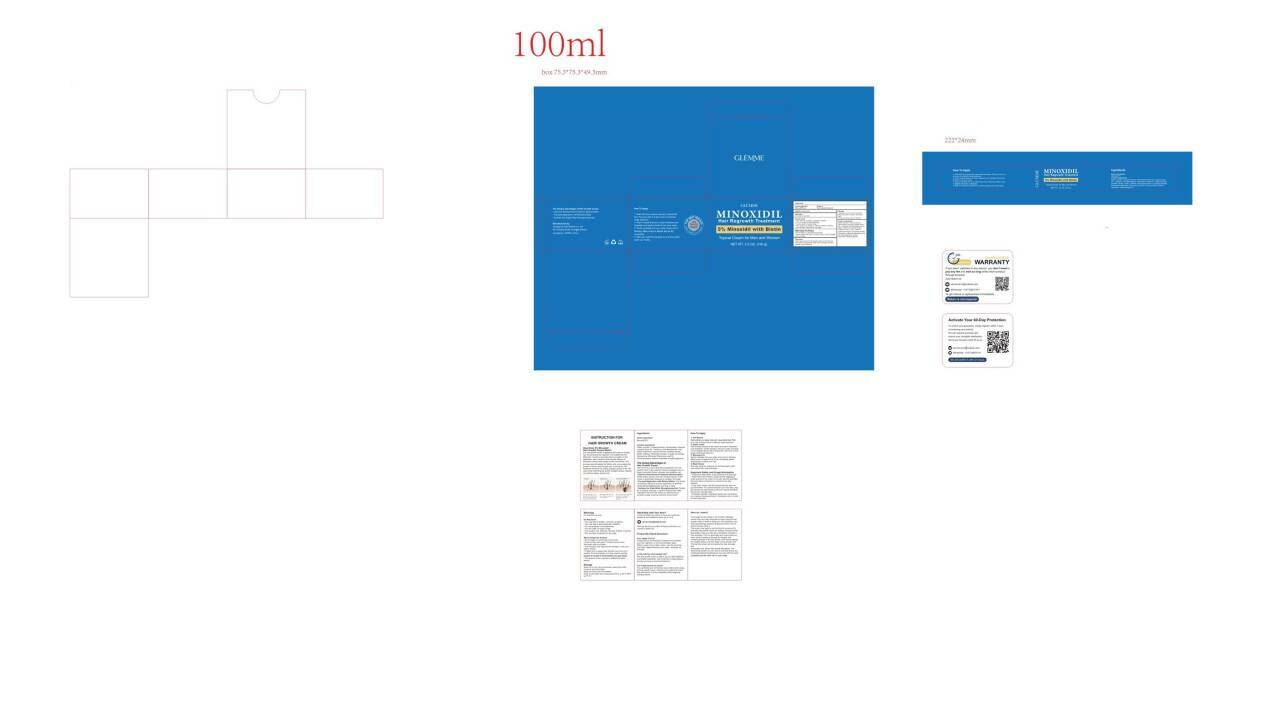 DRUG LABEL: GLEMME 5% Minoxidil Hair Regrowth Cream
NDC: 84148-016 | Form: CREAM
Manufacturer: Guangzhou Ariel Biotech Co., Ltd.
Category: otc | Type: HUMAN OTC DRUG LABEL
Date: 20251204

ACTIVE INGREDIENTS: MINOXIDIL 5 g/100 g
INACTIVE INGREDIENTS: GLYCERIN; CETEARYL ALCOHOL; SIMMONDSIA CHINENSIS (JOJOBA) SEED OIL; TREHALOSE; ALOE VERA LEAF OIL; PANTHENOL; CETEARYL OLIVATE; SORBITAN OLIVATE; BIOTIN; CAFFEINE; ALPHA-TOCOPHEROL ACETATE; ROSMARINUS OFFICINALIS (ROSEMARY) LEAF OIL; PHENOXYETHANOL; SODIUM HYDROXIDE; ETHYLHEXYLGLYCERIN; WATER

84148-016

Active Ingredient(s)

Minoxidil 5% w/v

Purpose

Hair regrowth treatment

Use

Use(s) to regrow hair

Warnings

For external use only.

Do not use

·Your hair loss is sudden, uncertain or patchy.
.You are pregnant or breastfeeding.
.You are under 18 years of age.
.Your scalp is red, inflamed, infected, irritated, or painful.
·You use other medicines on the scalp.

WHEN USING

. Do not apply on other parts of the body.
.Avoid contact with eyes. If contact occurs, rinse thoroughly with cool water.

Discontinue use if redness or irritation occurs.

Keep out of reach of children.

Directions

Apply right amount of hair growth cream on the hair loss
area, gently massage the scalp with your fingers until the
product is fully absorbed.

Other information

Store it in a cool, dry environment, away from heat, moisture, and direct light.

Inactive ingredients

Water, Glycerin, Cetearyl Alcohol, Simmondsia Chinensis (Jojoba) Seed Oil，Trehalose, Aloe Barbadensis Leaf
Water, Panthenol, Ceteary| Olivate, Sorbitan Olivate，Biotin, Caffeine, Hydrolyzed Keratin, Tocophery| Acetate,
Rosmarinus Officinalis(Rosemary) Leaf Oil, Phenoxyethanol,Sodium Hydroxide, Ethylhexylglycerin.